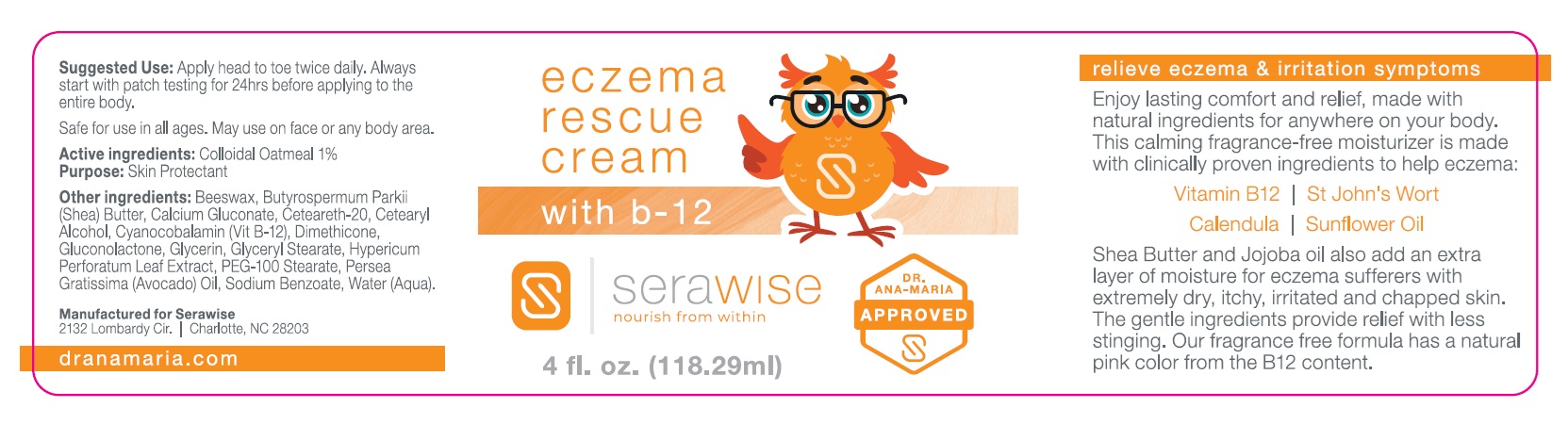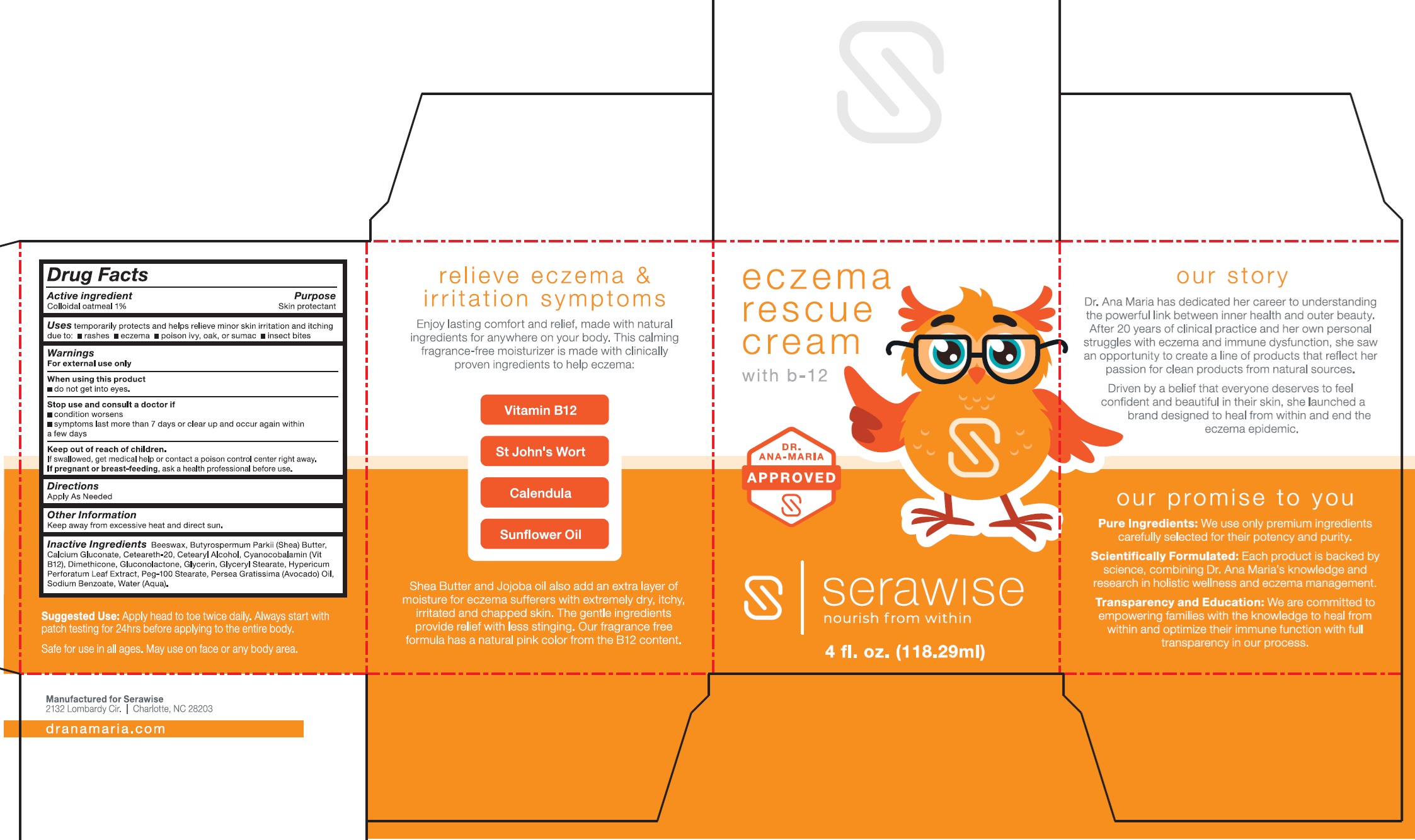 DRUG LABEL: Serawise Eczema Rescue
NDC: 85050-575 | Form: CREAM
Manufacturer: DrAnaMaria.com LLC
Category: otc | Type: HUMAN OTC DRUG LABEL
Date: 20241218

ACTIVE INGREDIENTS: OATMEAL 10 mg/1 mL
INACTIVE INGREDIENTS: BEESWAX; SHEA BUTTER; CALCIUM GLUCONATE; CETEARETH-20; CETEARYL ALCOHOL; CYANOCOBALAMIN; DIMETHICONE; GLUCONOLACTONE; GLYCERIN; GLYCERYL STEARATE; HYPERICUM PERFORATUM LEAF; PEG-100 STEARATE; PERSEA GRATISSIMA (AVOCADO) OIL; SODIUM BENZOATE; WATER

Serawise Eczema Rescue Cream

Active ingredient

Colloidal oatmeal 1%

Purpose

Skin protectant

Uses

temporarily protects and helps relieve minor skin irritation and itching duee to:

- rashes
- eczema
- poison ivy, oak, or sumac
- insect bites

Warnings

For external use only

When using this product

- do not get into eyes.

Stop use and consult a doctor if

- condition worsens
- symptoms last more than 7 days or clear up and occur again within a few days

Keep out of reach of children.

If swallowed, get medical help or contact a poison control center right away.

If pregnant or breast-feeding,

ask a health professional before use.

Directions

Apply as Needed

Other Information

Keep away from excessive heat and direct sun.

Inactive Ingredients

Beeswax, Butyrospermum Parkii (Shea) Butter, Calcium Gluconate, Ceteareth-20, Cetearyl Alcohol, Cyanocobalamin (VitB12), Dimethicone, Gluconolactone, Glycerin, Glyceryl Stearate, Hypericum Perforatum Leaf Extract, Peg-100 Stearate, Persea Gratissima (Avocado) Oil, Sodium Benzoate, Water (Aqua).